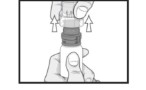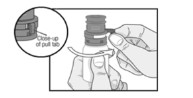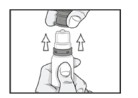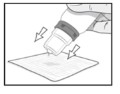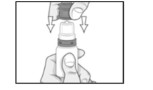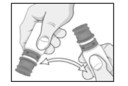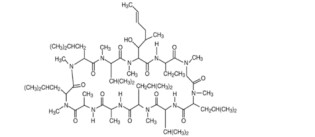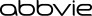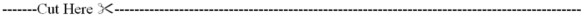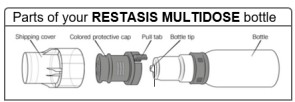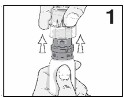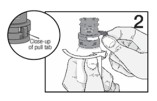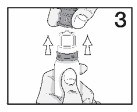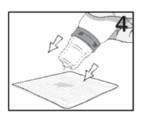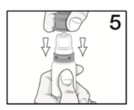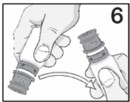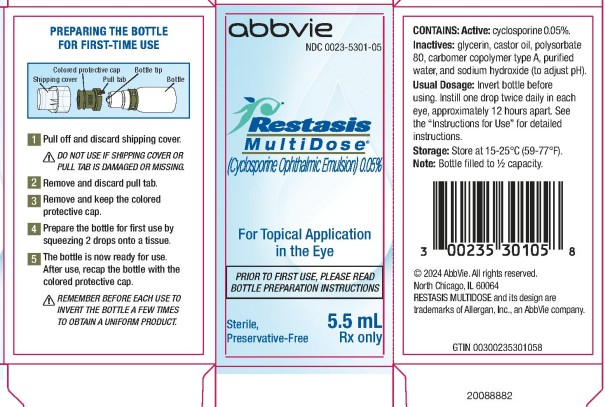 DRUG LABEL: Restasis MultiDose
NDC: 0023-5301 | Form: EMULSION
Manufacturer: Allergan, Inc.
Category: prescription | Type: HUMAN PRESCRIPTION DRUG LABEL
Date: 20250821

ACTIVE INGREDIENTS: CYCLOSPORINE 0.5 mg/1 mL
INACTIVE INGREDIENTS: GLYCERIN; CASTOR OIL; POLYSORBATE 80; CARBOMER COPOLYMER TYPE A; WATER; SODIUM HYDROXIDE

HIGHLIGHTS OF PRESCRIBING INFORMATION

These highlights do not include all the information needed to use RESTASIS MULTIDOSE safely and effectively. See full prescribing information for RESTASIS MULTIDOSE.
RESTASIS MULTIDOSE® (cyclosporine ophthalmic emulsion) 0.05%, for topical ophthalmic use
Initial U.S. Approval: 1983

1 INDICATIONS AND USAGE

RESTASIS MULTIDOSE is a calcineurin inhibitor immunosuppressant indicated to increase tear production in patients whose tear production is presumed to be suppressed due to ocular inflammation associated with keratoconjunctivitis sicca. Increased tear production was not seen in patients currently taking topical anti-inflammatory drugs or using punctal plugs. (1)

2 DOSAGE AND ADMINISTRATION

- Prime by squeezing two drops onto a tissue before initial use. (2.1)
- Instill one drop of RESTASIS MULTIDOSE ophthalmic emulsion twice a day in each eye approximately 12 hours apart. (2.2)

3 DOSAGE FORMS AND STRENGTHS

Cyclosporine ophthalmic emulsion 0.05% (0.5 mg/mL) (3)

4 CONTRAINDICATIONS

- Hypersensitivity (4)

5 WARNINGS AND PRECAUTIONS

- To avoid the potential for eye injury and contamination, be careful not to touch the bottle tip to your eye or other surfaces. (5.1)

6 ADVERSE REACTIONS

The most common adverse reaction following the use of cyclosporine ophthalmic emulsion 0.05% was ocular burning (17%). (6.1)

To report SUSPECTED ADVERSE REACTIONS, contact AbbVie at 1-800-633-9110 or FDA at 1-800-FDA-1088 or www.fda.gov/medwatch.

FULL PRESCRIBING INFORMATION

1 INDICATIONS AND USAGE

RESTASIS MULTIDOSE® ophthalmic emulsion is indicated to increase tear production in patients whose tear production is presumed to be suppressed due to ocular inflammation associated with keratoconjunctivitis sicca. Increased tear production was not seen in patients currently taking topical anti-inflammatory drugs or using punctal plugs.

2 DOSAGE AND ADMINISTRATION

Instill one drop of RESTASIS MULTIDOSE ophthalmic emulsion twice a day in each eye approximately 12 hours apart. RESTASIS MULTIDOSE can be used concomitantly with lubricant eye drops, allowing a 15-minute interval between products.

2.1 Preparation for First-Time Use

Step 1: Pull off the clear shipping cover by pulling straight up. Throw the shipping cover away. Do not use RESTASIS MULTIDOSE if shipping cover or pull tab are damaged or missing.

Step 2: Remove the pull tab on the olive green colored protective cap by pulling the end of the pull tab away from the bottle then winding it counterclockwise. Throw away the pull tab.

Step 3: Remove the olive green colored protective cap by pulling it straight up. Keep the colored protective cap.

Step 4: Prime the bottle for first-time use by squeezing two drops onto a tissue. Do not let the bottle tip touch the tissue.

Step 5: The bottle is now ready for use. After use, recap the bottle with the olive green colored protective cap by pushing it straight down onto the bottle.

2.2 Preparation for Use

Step 6: Turn the bottle upside down a few times before giving your dose to make sure the medicine is mixed well.

Step 7: Instill one drop in the affected eye. Replace the olive green colored protective cap.

3 DOSAGE FORMS AND STRENGTHS

Ophthalmic emulsion containing cyclosporine 0.05% (0.5 mg/mL)

4 CONTRAINDICATIONS

RESTASIS MULTIDOSE is contraindicated in patients with known or suspected hypersensitivity to any of the ingredients in the formulation [see Adverse Reactions (6.2)].

5 WARNINGS AND PRECAUTIONS

5.1 Potential for Eye Injury and Contamination

Be careful not to touch the bottle tip to your eye or other surfaces to avoid potential for eye injury and contamination.

5.2 Use with Contact Lenses

RESTASIS MULTIDOSE should not be administered while wearing contact lenses. Patients with decreased tear production typically should not wear contact lenses. If contact lenses are worn, they should be removed prior to the administration of the emulsion. Lenses may be reinserted 15 minutes following administration of RESTASIS MULTIDOSE ophthalmic emulsion.

6 ADVERSE REACTIONS

The following serious adverse reactions are described elsewhere in the labeling:

- Potential for Eye Injury and Contamination [see Warnings and Precautions (5.1)]

6.1 Clinical Trials Experience

Because clinical trials are conducted under widely varying conditions, adverse reaction rates observed in the clinical trials of a drug cannot be directly compared to rates in the clinical trials of another drug and may not reflect the rates observed in practice.

In clinical trials, the most common adverse reaction following the use of cyclosporine ophthalmic emulsion, 0.05% was ocular burning (17%).

Other reactions reported in 1% to 5% of patients included conjunctival hyperemia, discharge, epiphora, eye pain, foreign body sensation, pruritus, stinging, and visual disturbance (most often blurring).

6.2 Post-marketing Experience

The following adverse reactions have been identified during post approval use of cyclosporine ophthalmic emulsion, 0.05%. Because these reactions are reported voluntarily from a population of uncertain size, it is not always possible to reliably estimate their frequency or establish a causal relationship to drug exposure.

Reported reactions have included: hypersensitivity (including eye swelling, urticaria, rare cases of severe angioedema, face swelling, tongue swelling, pharyngeal edema, and dyspnea); and superficial injury of the eye (from the bottle tip touching the eye during administration).

8 USE IN SPECIFIC POPULATIONS

8.1 Pregnancy

Risk Summary
Clinical administration of cyclosporine ophthalmic emulsion 0.05% is not detected systemically following topical ocular administration [see Clinical Pharmacology (12.3)], and maternal use is not expected to result in fetal exposure to the drug. Oral administration of cyclosporine to pregnant rats or rabbits did not produce teratogenicity at clinically relevant doses [see Data].

Data
Animal Data
At maternally toxic doses (30 mg/kg/day in rats and 100 mg/kg/day in rabbits), cyclosporine oral solution (USP) was teratogenic as indicated by increased pre- and postnatal mortality, reduced fetal weight and skeletal retardations. These doses (normalized to body surface area) are 5,000 and 32,000 times greater, respectively, than the daily recommended human dose of one drop (approximately 28 mcL) of cyclosporine ophthalmic emulsion 0.05% twice daily into each eye of a 60 kg person (0.001 mg/kg/day), assuming that the entire dose is absorbed. No evidence of embryofetal toxicity was observed in rats or rabbits receiving cyclosporine during organogenesis at oral doses up to 17 mg/kg/day or 30 mg/kg/day, respectively. These doses in rats and rabbits are approximately 3,000 and 10,000 times greater, respectively, than the daily recommended human dose.

An oral dose of 45 mg/kg/day cyclosporine administered to rats from Day 15 of pregnancy until Day 21 postpartum produced maternal toxicity and an increase in postnatal mortality in offspring. This dose is 7,000 times greater than the daily recommended human dose. No adverse effects in dams or offspring were observed at oral doses up to 15 mg/kg/day (2,000 times greater than the daily recommended human dose).

8.2 Lactation

Risk Summary
Cyclosporine is known to appear in human milk following systemic administration, but its presence in human milk following topical treatment has not been investigated. Although blood concentrations are undetectable following topical administration of cyclosporine ophthalmic emulsion 0.05% [see Clinical Pharmacology (12.3)], caution should be exercised when RESTASIS MULTIDOSE is administered to a nursing woman. The developmental and health benefits of breastfeeding should be considered along with the mother’s clinical need for RESTASIS MULTIDOSE and any potential adverse effects on the breast-fed child from cyclosporine.

8.4 Pediatric Use

Safety and efficacy have not been established in pediatric patients below the age of 16.

8.5 Geriatric Use

No overall difference in safety or effectiveness has been observed between elderly and younger patients.

11 DESCRIPTION

RESTASIS MULTIDOSE (cyclosporine ophthalmic emulsion) 0.05% contains a calcineurin inhibitor immunosuppressant with anti-inflammatory effects. Cyclosporine’s chemical name is Cyclo[[(E)-(2S,3R,4R)-3-hydroxy-4-methyl-2-(methylamino)-6-octenoyl]-L-2-aminobutyryl-N-methylglycyl-N-methyl-L-leucyl-L-valyl-N-methyl-L-leucyl-L-alanyl-D-alanyl-N-methyl-L-leucyl-N-methyl-L-leucyl-N-methyl-L-valyl] and it has the following structure:

Structural Formula

Formula: C62H111N11O12 Mol. Wt.: 1202.6

Cyclosporine is a fine white powder. RESTASIS MULTIDOSE appears as a white opaque to slightly translucent homogeneous emulsion. It has an osmolality of 230 to 320 mOsmol/kg and a pH of 6.5-8.0. Each mL of RESTASIS MULTIDOSE ophthalmic emulsion contains: Active: cyclosporine 0.05%. Inactives: glycerin; castor oil; polysorbate 80; carbomer copolymer type A; purified water; and sodium hydroxide to adjust pH. RESTASIS MULTIDOSE contains no preservatives.

12 CLINICAL PHARMACOLOGY

12.1 Mechanism of Action

Cyclosporine is an immunosuppressive agent when administered systemically.

In patients whose tear production is presumed to be suppressed due to ocular inflammation associated with keratoconjunctivitis sicca, cyclosporine emulsion is thought to act as a partial immunomodulator. The exact mechanism of action is not known.

12.3 Pharmacokinetics

Blood cyclosporine A concentrations were measured using a specific high pressure liquid chromatography-mass spectrometry assay. Blood concentrations of cyclosporine, in all the samples collected, after topical administration of cyclosporine ophthalmic emulsion, 0.05%, twice daily, in humans for up to 12 months, were below the quantitation limit of 0.1 ng/mL. There was no detectable drug accumulation in blood during 12 months of treatment with cyclosporine ophthalmic emulsion, 0.05%.

13 NONCLINICAL TOXICOLOGY

13.1 Carcinogenesis, Mutagenesis, Impairment of Fertility

Carcinogenesis
Systemic carcinogenicity studies were conducted in male and female mice and rats. In the 78-week oral (diet) mouse study, at doses of 1, 4, and 16 mg/kg/day, evidence of a statistically significant trend was found for lymphocytic lymphomas in females, and the incidence of hepatocellular carcinomas in mid-dose males significantly exceeded the control value.

In the 24-month oral (diet) rat study, conducted at 0.5, 2, and 8 mg/kg/day, pancreatic islet cell adenomas significantly exceeded the control rate in the low dose level. The hepatocellular carcinomas and pancreatic islet cell adenomas were not dose related. The low doses in mice and rats are approximately 80 times greater (normalized to body surface area) than the daily recommended human dose of one drop (approximately 28 mcL) of cyclosporine ophthalmic emulsion, 0.05% twice daily into each eye of a 60 kg person (0.001 mg/kg/day), assuming that the entire dose is absorbed.

Mutagenesis
Cyclosporine has not been found to be mutagenic/genotoxic in the Ames Test, the V79-HGPRT Test, the micronucleus test in mice and Chinese hamsters, the chromosome-aberration tests in Chinese hamster bone-marrow, the mouse dominant lethal assay, and the DNA-repair test in sperm from treated mice. A study analyzing sister chromatid exchange (SCE) induction by cyclosporine using human lymphocytes in vitro gave indication of a positive effect (i.e., induction of SCE).

Impairment of Fertility
No impairment in fertility was demonstrated in studies in male and female rats receiving oral doses of cyclosporine up to 15 mg/kg/day (approximately 2,000 times the human daily dose of 0.001 mg/kg/day normalized to body surface area) for 9 weeks (male) and 2 weeks (female) prior to mating.

14 CLINICAL STUDIES

Four multicenter, randomized, adequate and well-controlled clinical studies were performed in approximately 1,200 patients with moderate to severe keratoconjunctivitis sicca. Cyclosporine ophthalmic emulsion, 0.05% demonstrated statistically significant increases in Schirmer wetting of 10 mm versus vehicle at six months in patients whose tear production was presumed to be suppressed due to ocular inflammation. This effect was seen in approximately 15% of cyclosporine ophthalmic emulsion, 0.05%-treated patients versus approximately 5% of vehicle-treated patients. Increased tear production was not seen in patients currently taking topical anti-inflammatory drugs or using punctal plugs.

No increase in bacterial or fungal ocular infections was reported following administration of cyclosporine ophthalmic emulsion, 0.05%.

16 HOW SUPPLIED/STORAGE AND HANDLING

RESTASIS MULTIDOSE ophthalmic emulsion is packaged in a sterile, multi-dose bottle. Each bottle consists of a white opaque LDPE bottle, a white opaque polypropylene top with unidirectional valve and air filter, a protective olive green polypropylene cap, and a clear disposable shipping cover over the colored cap. RESTASIS MULTIDOSE contains no preservatives.

5.5 mL in 10-mL bottle - NDC 0023-5301-05

Storage: Store at 15°C to 25°C (59°F to 77°F). After opening, RESTASIS MULTIDOSE can be used until the expiration date on the bottle.

17 PATIENT COUNSELING INFORMATION

Advise the patient to read the FDA-approved patient labeling (Instructions for Use).

Handling the Container

Advise patients to not allow the tip of the bottle to touch the eye or any surface, as this may contaminate the emulsion. Advise patients to not touch the bottle tip to their eye to avoid the potential for injury to the eye [see Warnings and Precautions (5.1)].

Use with Contact Lenses

RESTASIS MULTIDOSE should not be administered while wearing contact lenses. Patients with decreased tear production typically should not wear contact lenses. Advise patients that if contact lenses are worn, they should be removed prior to the administration of the emulsion. Lenses may be reinserted 15 minutes following administration of RESTASIS MULTIDOSE ophthalmic emulsion [see Warnings and Precautions (5.2)].

Administration

Advise patients to read the “Instructions for Use” for detailed first-time use instructions.

Distributed by:
AbbVie Inc.
North Chicago, IL 60064

© 2025 AbbVie. All rights reserved.
RESTASIS MULTIDOSE and its design are trademarks of Allergan, Inc., an AbbVie company.

v2.0USPI5301

PATIENT INFORMATION

INSTRUCTIONS FOR USE
RESTASIS MULTIDOSE® (Re stay’ sis Mul tee dōs)
(cyclosporine ophthalmic emulsion) 0.05%

Read this Instructions for Use before you start using RESTASIS MULTIDOSE and each time you get a refill. There may be new information. This leaflet does not take the place of talking to your healthcare provider about your medical condition or treatment.

Important:

- RESTASIS MULTIDOSE is for use in the eye
- Wash your hands before using RESTASIS MULTIDOSE.
- Do not let the bottle tip touch the eye or any other surfaces to avoid contamination or injury to your eye.
- Use 1 drop of RESTASIS MULTIDOSE in each eye, 2 times each day, about 12 hours apart.
- If you wear contact lenses, remove them before using RESTASIS MULTIDOSE. Wait for at least 15 minutes before placing them back in your eyes.
- RESTASIS MULTIDOSE can be used with lubricant eye drops, but you should wait at least 15 minutes between using each product.

PREPARING THE BOTTLE FOR FIRST-TIME USE:

Step 1: Pull off shipping cover by pulling straight up. Throw the shipping cover away. Do not use RESTASIS MULTIDOSE if shipping cover or pull tab are damaged or missing.

Step 2: Remove the pull tab on the olive green colored protective cap by pulling the end of the pull tab away from the bottle then winding it counterclockwise. Throw away the pull tab.

Step 3: Remove the olive green colored protective cap by pulling it straight up. Keep the colored protective cap.

Step 4: Prime the bottle for first time use by squeezing 2 drops onto a tissue. Do not let the bottle tip touch the tissue.

Step 5: The bottle is now ready for use. After use, recap the bottle with the olive green colored protective cap by pushing straight down onto the bottle.

GIVING YOUR DOSE:

Step 6: Turn the bottle upside down a few times before giving your dose to make sure the medicine is mixed well.

Step 7: Instill one drop in the affected eye. Replace the olive green colored protective cap.

How do I store RESTASIS MULTIDOSE?

- Store RESTASIS MULTIDOSE between 15°C to 25°C (59°F to 77°F).
- After opening, RESTASIS MULTIDOSE can be used until the expiration date (EXP) on the bottle.

Keep RESTASIS MULTIDOSE and all medicines out of the reach of children.

This Instructions for Use has been approved by the Food and Drug Administration.

Distributed by:
AbbVie Inc.
North Chicago, IL 60064

© 2025 AbbVie. All rights reserved.
RESTASIS MULTIDOSE and its design are trademarks of Allergan, Inc., an AbbVie company.

Approved: 8/2025
v2.0IFU5301

PRINCIPAL DISPLAY PANEL – Restasis Multidose Carton Label

NDC 0023-5301-05
abbvie
Restasis
MultiDose™
(Cyclosporine Ophthalmic Emulsion) 0.05%
For Topical Application
In the Eye
PRIOR TO FIRST USE, PLEASE READ
BOTTLE PREPARATION INSTRUCTIONS
Sterile, 5.5 mL
Preservative-Free Rx Only